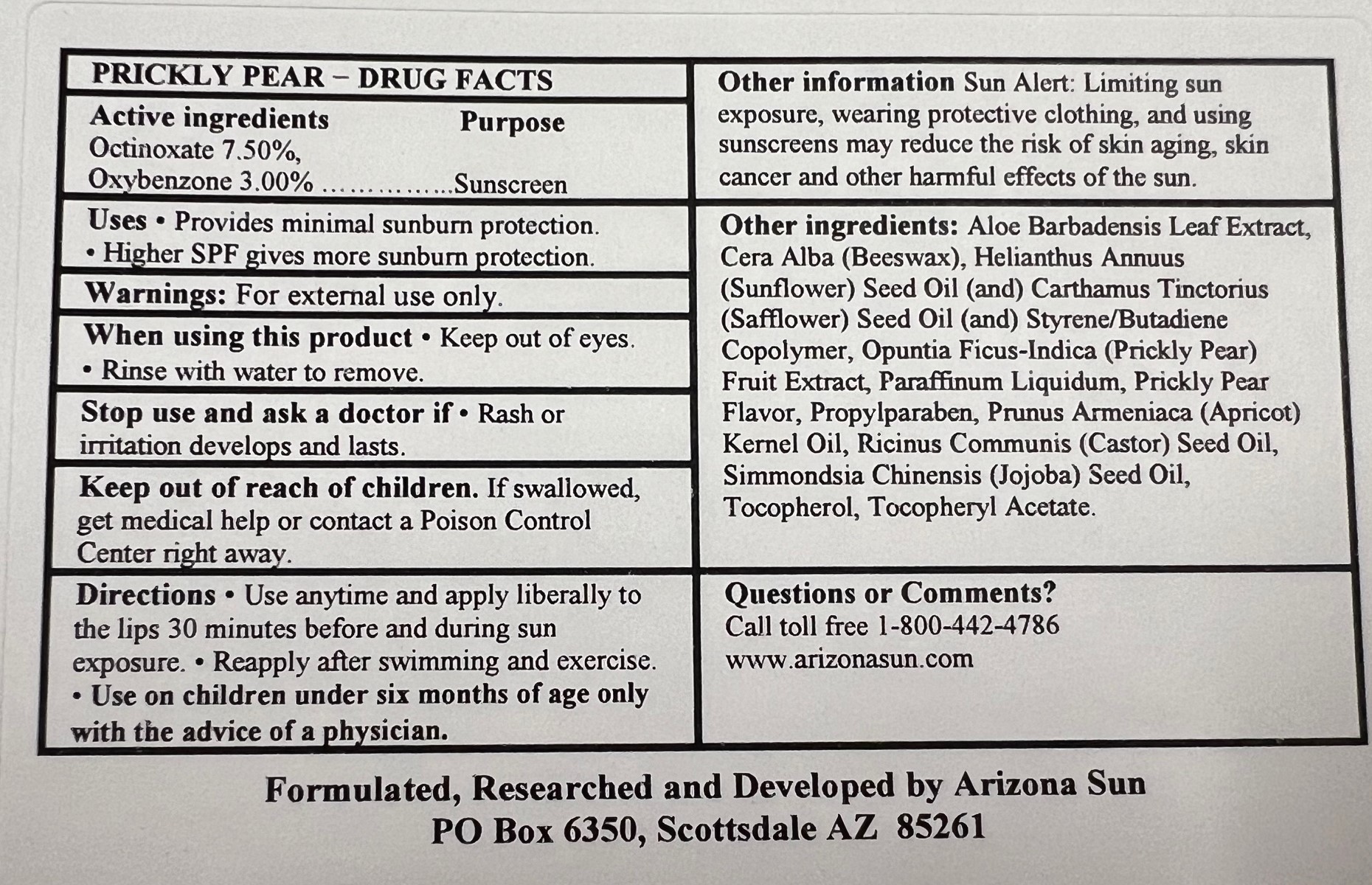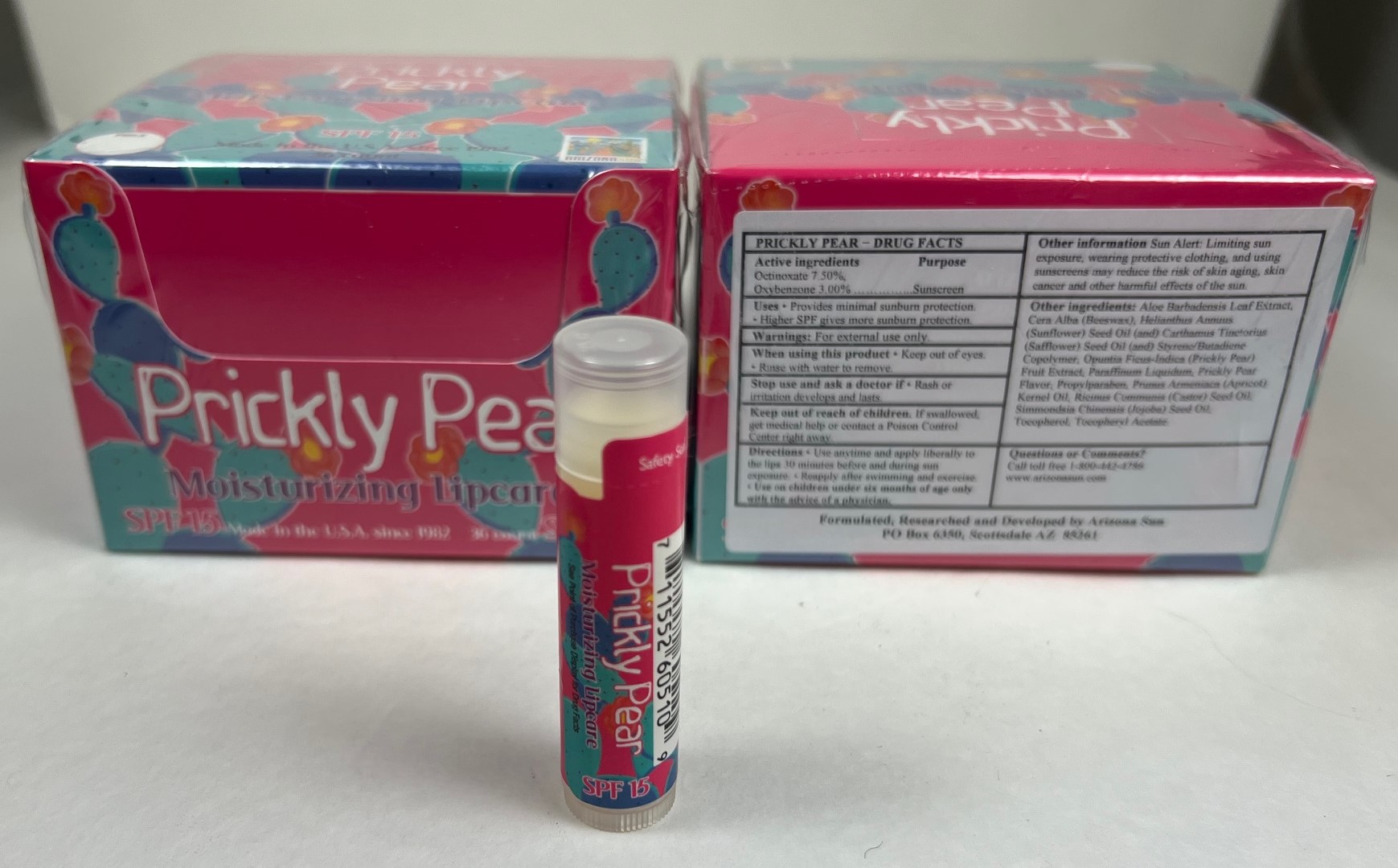 DRUG LABEL: Arizona Sun Prickly Pear Lip Balm SPF 15
NDC: 61973-400 | Form: LIPSTICK
Manufacturer: Arizona Sun Products
Category: otc | Type: HUMAN OTC DRUG LABEL
Date: 20240223

ACTIVE INGREDIENTS: OCTINOXATE 75 mg/1 g; OXYBENZONE 30 mg/1 g
INACTIVE INGREDIENTS: PRICKLY PEAR FRUIT; TOCOPHEROL; OPUNTIA FICUS-INDICA FRUIT JUICE; PROPYLPARABEN; SAFFLOWER OIL; ALOE VERA LEAF; MINERAL OIL; CASTOR OIL; SUNFLOWER SEED; SIMMONDSIA CHINENSIS SEED; .ALPHA.-TOCOPHEROL ACETATE; WHITE WAX; APRICOT KERNEL OIL

Prickly Pear Lip Balm

Active Ingredients

Octinoxate 7.50%, Oxybenzone 3.00%

Purpose

Sunscreen

Uses

Provides moderate sunburn protection. Higher SPF gives more sunburn protection

Warnings

For external use only.

When using this product

keep out of eyes. Rinse with water to remove

Stop use and ask a doctor if

rash or irritation develops and lasts.

Keep out of the reach of children.

If swallowed get medical help or contact a poison control center right away.

Directions

Use anytime and apply liberally to the lips 30 minutes before and during sun exposure. Reapply after swimming and exercise. Use on children under the age of six months only wih the advise of a physician.

Other Information

Sun Alert: Limiting sun exposure, wearing protective clothing, and using suscreen may reduce the risk of skin aging, skin cancer and other harmful effects of the sun.

Inactive Ingredients

Aloe Barbadensis Leaf (Aloe Vera) Extract, Cera Alba (Beeswax), Helianthus Annuus (Sunflower) Seed Oil, Carthamus Tinctorius (Safflower) Seed Oil, Styrene/Butadiene Copolymer, Opuntia Ficus-Indica (Prickly Pear) Fruit Extract, Paraffinum Liquidum, Prickly Pear Flavor, Propylparaben, Prunus Armeniaca (Apricot) Kernel Oil, Ricinus Communis (Castor) Seed Oil, Simmondsia Chinensis (Jojoba) Seed Oil, Tocopherol, Tocopheryl Acetate

Questions or Comments?

Call toll free 1-800-442-4786